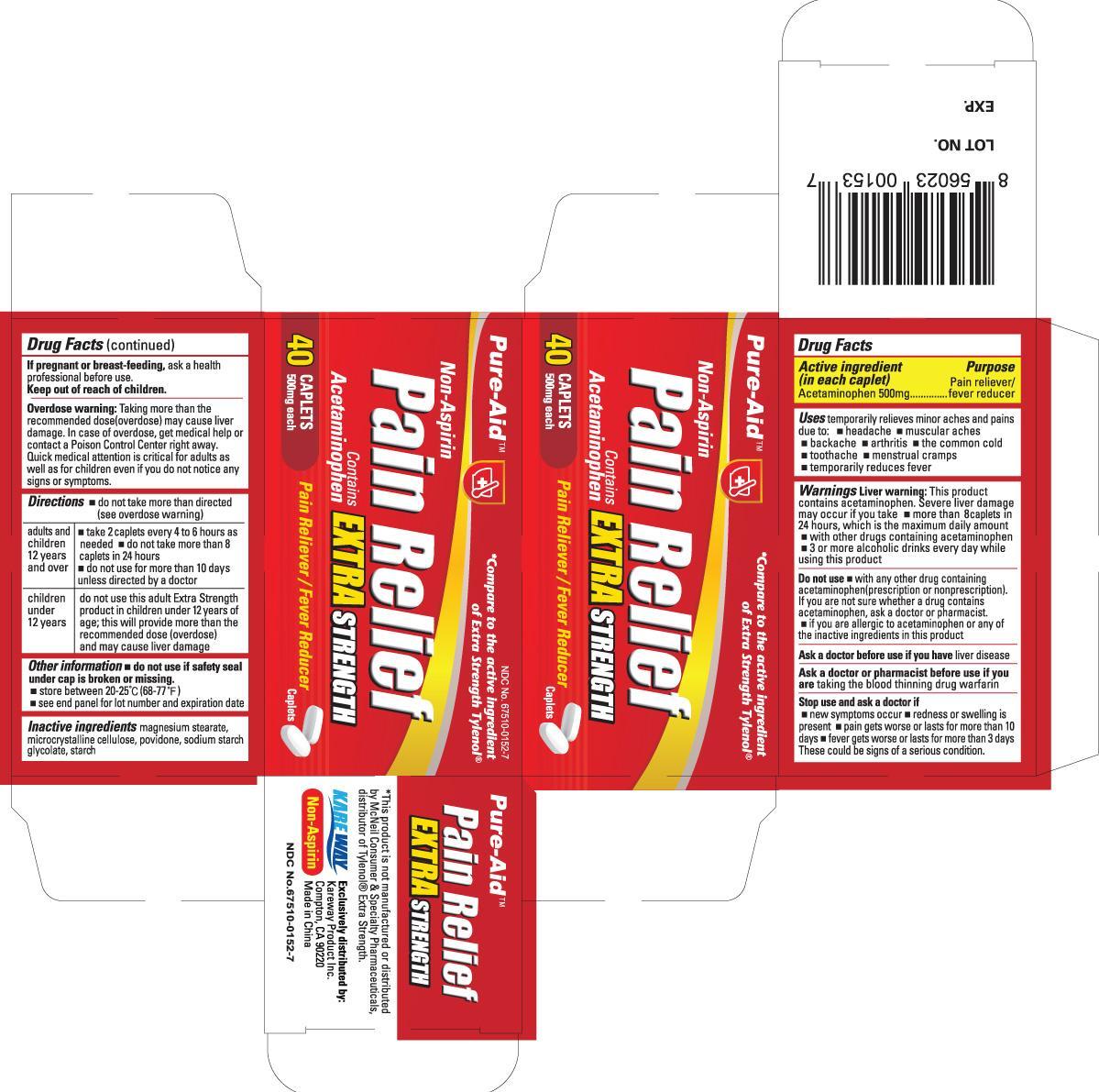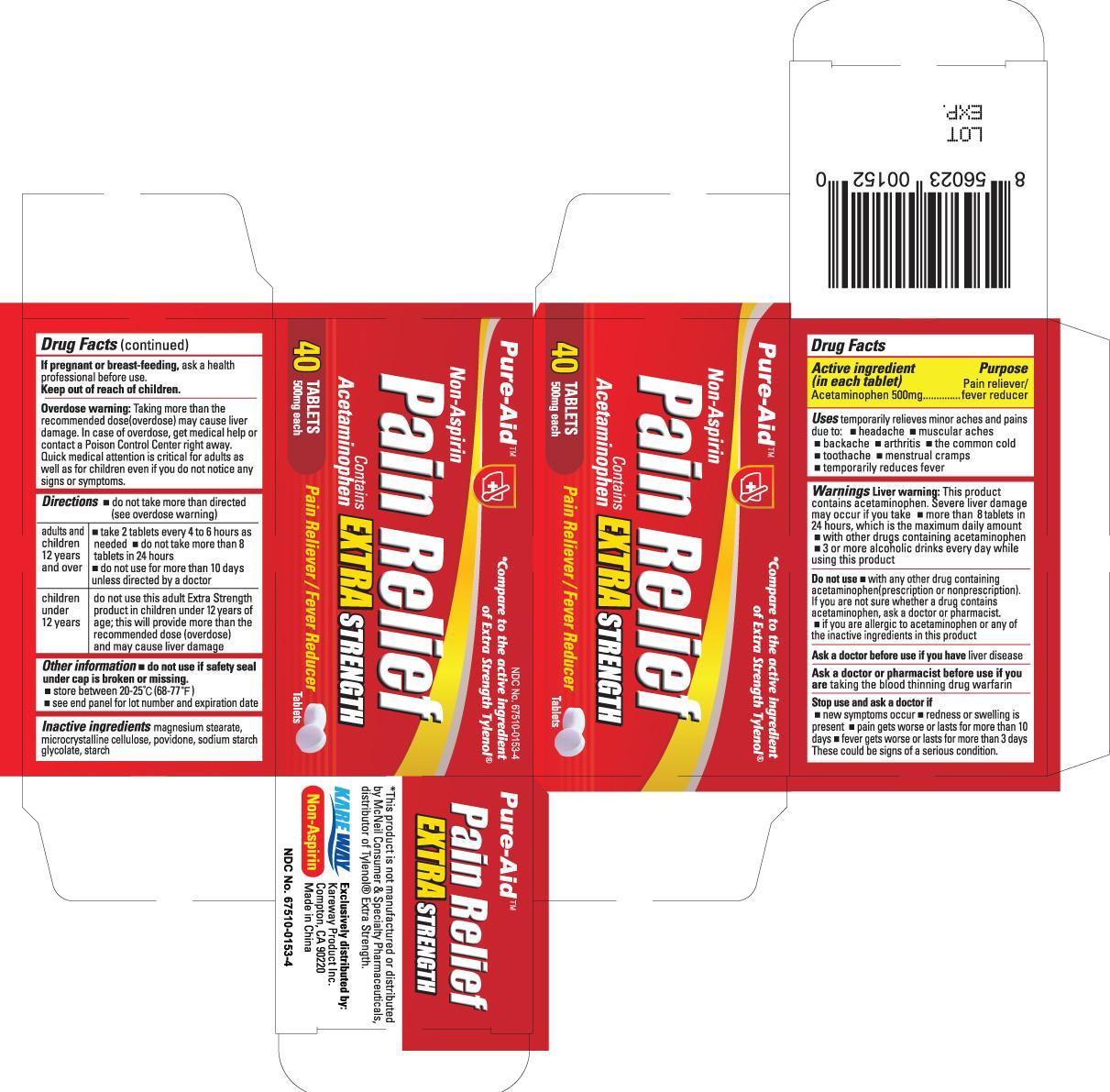 DRUG LABEL: Acetaminophen
NDC: 67510-0153 | Form: TABLET
Manufacturer: Kareway Product, Inc.
Category: otc | Type: HUMAN OTC DRUG LABEL
Date: 20130802

ACTIVE INGREDIENTS: ACETAMINOPHEN 500 mg/1 1
INACTIVE INGREDIENTS: ICODEXTRIN; STARCH, CORN; SODIUM LAURYL SULFATE; HYDROXYPROPYL CELLULOSE

Drug Facts

Active Ingredients (in each tablet)

Acetaminophen 500mg

Purpose

Pain Reliever/fever reducer

Warnings

Liver Warning:

this product contains acetaminophen. Severe liver damage may occur if you take

- more than 8 tablets in 24 hours, which is the maxium daily amount
- with other drugs containing acetaminophen
- 3 or more alcoholic drinks every day while using this product

Do not use

- with any other drug containing acetaminophen (prescription or nonprescription). If you are not sure whether a drug contains acetaminophen, ask a doctor or pharmacist.
- if you are allergic to acetaminophen or any of the inactive ingredients in this product

Ask a doctor before use if you have

liver disease

Ask a doctor or pharmacist before use if you are

taking the blood thinning drug warfarin

Stop use and ask a doctor if

- new symptoms occur
- redness or swelling is present
- pain gets worse or lasts for more than 10 days
- fever gets worse or lasts for more than 3 days

These could be sign of a serious condition

If pregnant or breast-feeding

ask a health professional before use.

Keep out of reach of children.

Enter section text here

Overdose warning:

Taking more than the recommended dose(overdose) may cause liver damage. In case of overdose, get medical help or contact a Poison Control Center right away. Quick medical attention is critical for adults as well as for children even if you do not notice any signs or symptoms.

Directions

- do not take more than directed (see overdose warning)

adults and children 12 years and over | - take 2 tablets every 4 to 6 house as needed - do not take more than 8 tablets in 24 hours - do not use for more than 10 days unless directed by a doctor
children under 12 years | do not use this adult Extra Strength product in children under 6 years of age; this will provide more than the recommended dose (overdose) and may cause liver damage

Other Information

- do not use if imprinted safety seal under cap is broken or missing.
- Store at 15° - 30°C (59° - 86°F)
- see end panel for lot number and expiration date

Inactive Ingredients

benzalkonium chloride, boric acid, edetate disodium, purified water, sodium borate, and sodium chloride

Uses

temporarily relieves minor aches and pains due to:

- headache
- muscular aches
- backache
- arthritis
- the common cold
- toothache
- mentrual cramps
- temporarily reduces fever

Package label

Non-Aspirin Pain Relief Extra Strength 40 caplates

Package Label

Non-Aspirin Pain Relief Extra Strength 40 tablets